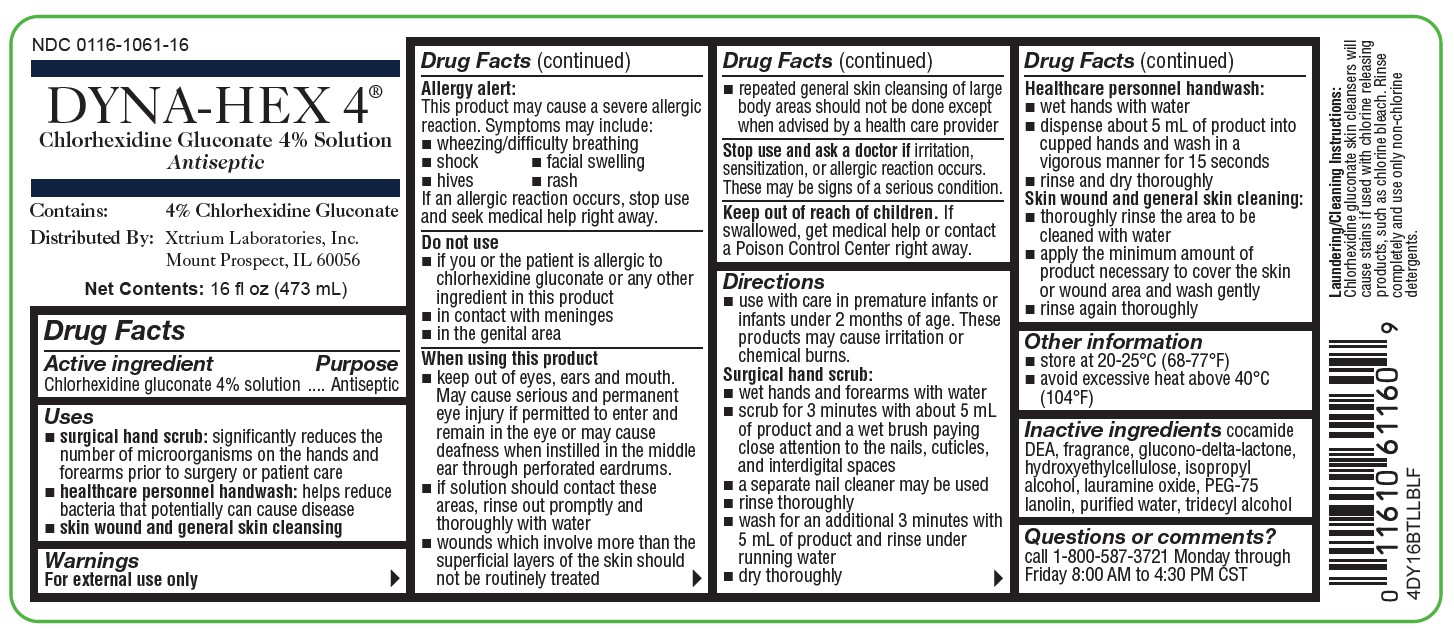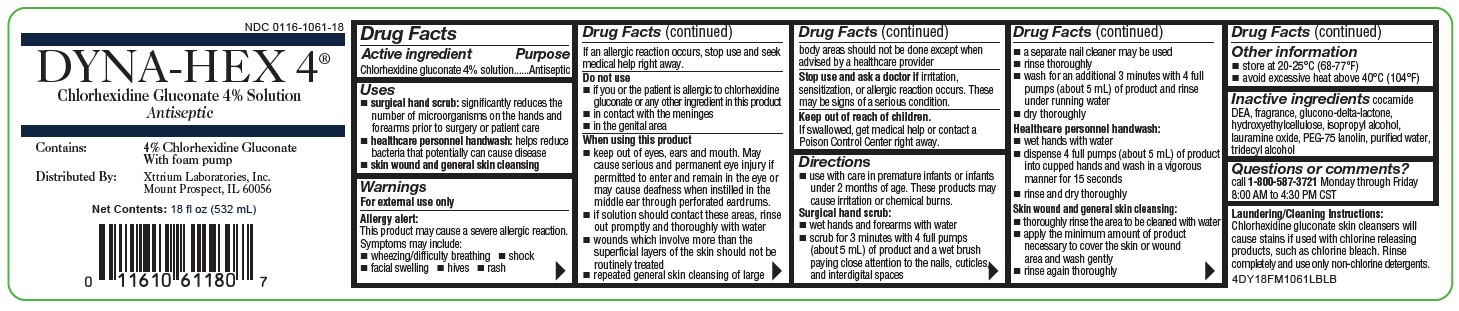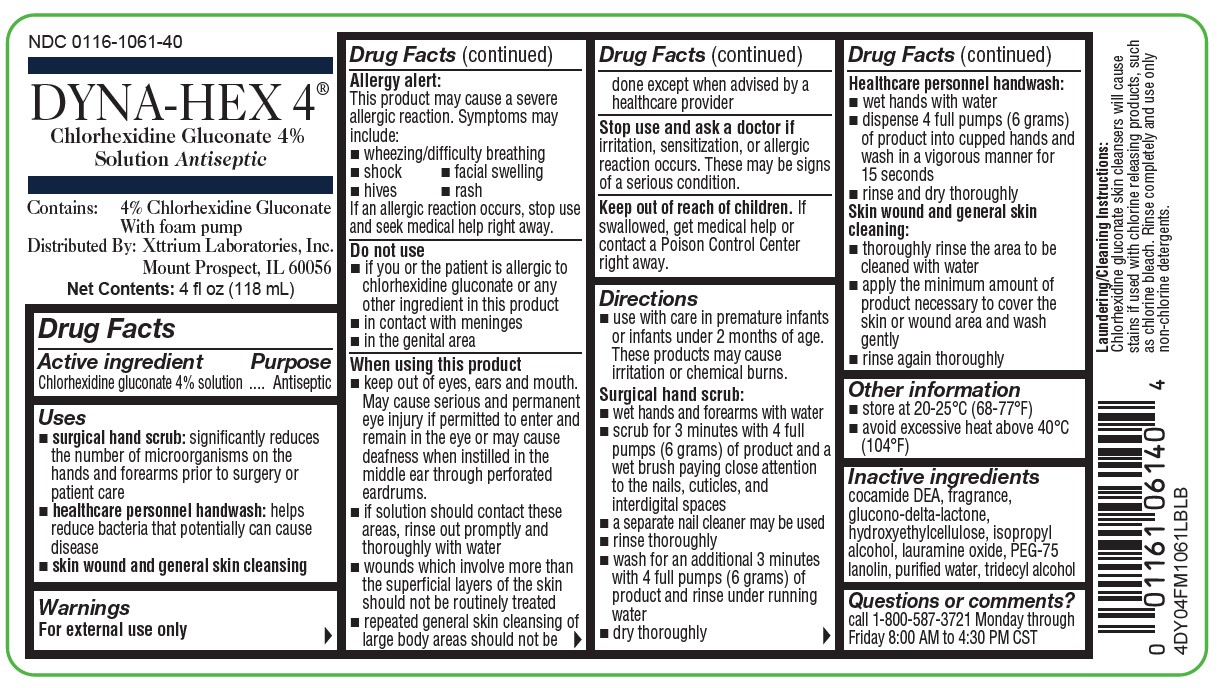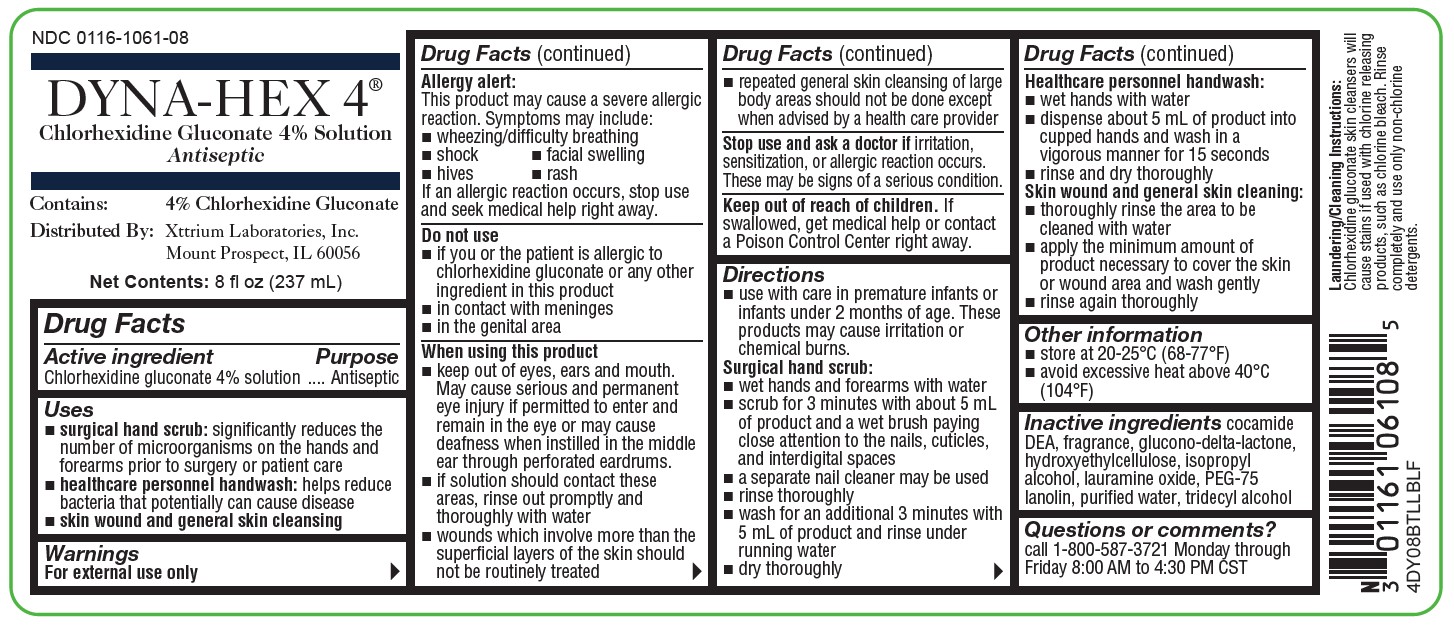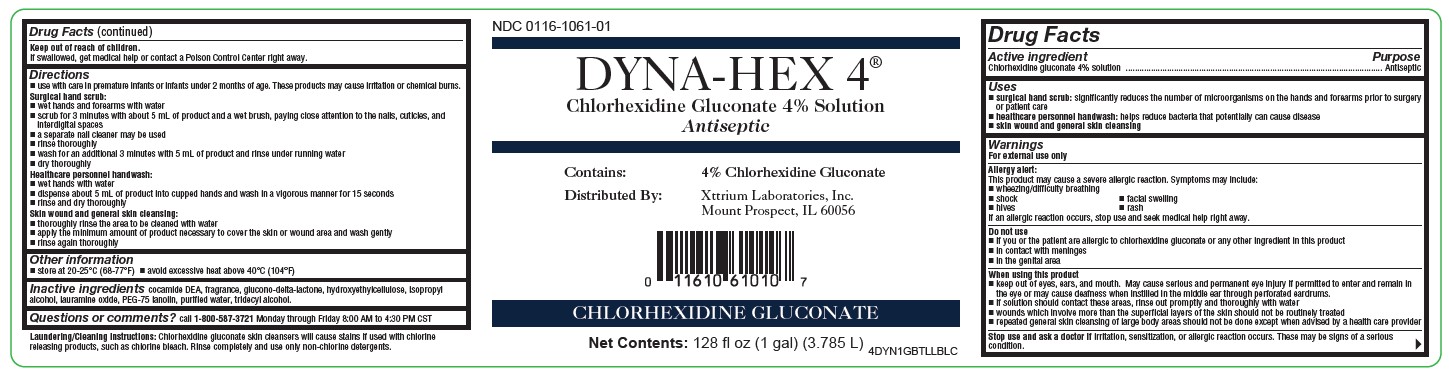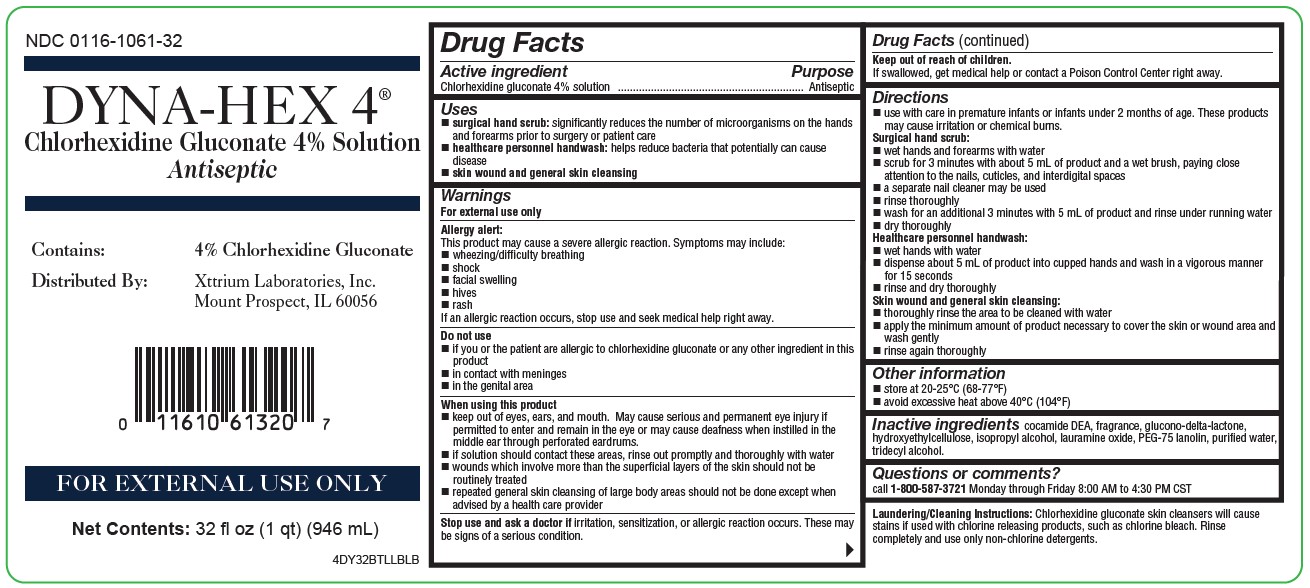 DRUG LABEL: ANTISEPTIC SKIN CLEANSER
NDC: 0116-1061 | Form: SOLUTION
Manufacturer: Xttrium Laboratories, Inc.
Category: otc | Type: HUMAN OTC DRUG LABEL
Date: 20251210

ACTIVE INGREDIENTS: CHLORHEXIDINE GLUCONATE 4 g/100 mL
INACTIVE INGREDIENTS: HYDROXYETHYL CELLULOSE (2000 CPS AT 1%); ISOPROPYL ALCOHOL; LAURAMINE OXIDE; WATER; TRIDECYL ALCOHOL; GLUCONOLACTONE; PEG-75 LANOLIN; COCO DIETHANOLAMIDE

Dyna-Hex 4: 4oz FM, 8oz, 16oz, 32oz, 1 Gallon
COMP 18ozFM

Active Ingredient

Chlorhexidine gluconate

Purpose

Antiseptic

Uses

- surgical hand scrub: significantly reduces the number of microorganisms on the hands and forearms prior to surgery or patient care
- healthcare personnel handwash: helps reduce bacteria that potentially can cause disease
- skin wound and general skin cleansing

Warnings

For external use only

Allergy alert:

This product may cause a severe allergic reaction. Symptoms may include:

- wheezing/difficulty breathing
- shock
- facial swelling
- hives
- rash

If an allergic reaction occurs, stop use and seek medical help right away.

Do not use

- if you or the patient is allergic to chlorhexidine gluconate or any other ingredient in this product
- in contact with meninges
- in the genital area
- as a preoperative skin preparation of the head or face (only in 4-oz)

When using this product

- keep out of eyes, ears and mouth. May cause serious and permanent eye injury if permitted to enter and remain in the eye or may cause deafness when instilled in the middle ear through perforated eardrums.
- if solution should contact these areas, rinse out promptly and thoroughly with water
- wounds which involve more than the superficial layers of the skin should not be routinely treated
- repeated general skin cleansing of large body areas should not be done except when advised by a health care provider

Stop use and ask a doctor if

irritation, sensitization, or allergic reaction occurs. These may be signs of a serious condition.

Keep out of reach of children.

If swallowed, get medical help or contact a Poison Control Center right away.

Do not use

- if you or the patient is allergic to chlorhexidine gluconate or any other ingredient in this product
- in contact with meninges
- in the genital area

When using this product

- keep out of eyes, ears, and mouth. May cause serious and permanent eye injury if permitted to enter and remain in the eye or may cause deafness when instilled in the middle ear through perforated eardrums.

- if solution should contact these areas, rinse out promptly and thoroughly with water

- wounds which involve more than the superficial layers of the skin should not be routinely treated
- repeated general skin cleansing of large body areas shold not be done except when advised by a health care provider

Stop use and ask doctor if

irritation, sensitization, or allergic reaction occurs. These may be signs of a serious condition

Keep out of reach of children

If swallowed, get medical help or contact a Poison Control Center right away.

Direction

- use with care in premature infants and infants under 2 months of age. These products may cause irritation or chemical burns.

Surgical hand scrub:

- wet hands and forearms with water
- scrub for 3 minutes with about 5 ml of product and a wet brush paying close attention to the nails, cuticles and interdigital spaces
- a separate nail cleaner may be used
- rinse thoroughly
- wash for an additional 3 minutes with 5 ml of product and rinse under running water
- dry thoroughly

Healthcare personnel handwash:

- wet hands with water
- dispense about 5 ml of product into cupped hands and wash in a vigorous manner for 15 seconds
- rinse and dry thoroughly

Skin wound and general skin cleaning:

- thoroughly rinse the area to be cleaned with water
- apply the minimum amount of product necessary to cover the skin or wound area and wash gently
- rinse again thoroughly

Other information

- store at 20-25ºC (68-77ºF)
- avoid excessive heat above 40ºC (104ºF)

Inactive ingredients

cocamide DEA, fragrance, glucono-delta-lactone, hydroxyethylcellulose, isopropyl alcohol, lauramine oxide, PEG-75 lanolin, purified water, tridecyl alcohol

Questions or comments?

call 1-800-587-3721 Monday through Friday 8:00 AM to 4:30 PM CST

Package label and principal display panel

NDC 0116-1061-08

DYNA-HEX 4 ®

(Chlorhexidine Gluconate 4% Solution)

Antiseptic

Contains: 4% Chlorhexidine Gluconate

Distributed by: Xttrium Laboratories, Inc., Mount Prospect, IL 60056

FOR EXTERNAL USE ONLY

Net Contents: 8 fl oz (237 mL)

4DY08BTLLBLF

NDC 0116-1061-16

DYNA-HEX 4 ®

(Chlorhexidine Gluconate 4% Solution)

Antiseptic

Contains: 4% Chlorhexidine Gluconate

Distributed by: Xttrium Laboratories, Inc., Mount Prospect, IL 60056

FOR EXTERNAL USE ONLY

Net Contents: 16 fl oz (473 mL)

4DY16BTLLBLF

NDC 0116-1061-32

DYNA-HEX 4 ®

(Chlorhexidine Gluconate 4% Solution)

Antiseptic

Contains: 4% Chlorhexidine Gluconate

Distributed by: Xttrium Laboratories, Inc., Mount Prospect, IL 60056

FOR EXTERNAL USE ONLY

Net Contents: 32 fl oz (946 mL)

4DY32BTLLBLB

NDC 0116-1061-01

DYNA-HEX 4 ®

(Chlorhexidine Gluconate 4% Solution)

Antiseptic

Contains: 4% Chlorhexidine Gluconate

Distributed by: Xttrium Laboratories, Inc., Mount Prospect, IL 60056

FOR EXTERNAL USE ONLY

Net Contents: 128 fl oz (1 gal)

4DYN1GBTLLBLC

NDC 0116-1061-40

DYNA-HEX 4®

Chlorhexidine Gluconate 4% Solution

Antiseptic

Contains:

4% Chlorhexidine Gluconate With foam pump

Distributed By:

Xttrium Laboratories, Inc.

Mount Prospect, IL 60056

FOR EXTERNAL USE ONLY

Net Contents: 4 fl oz (118mL)

4DY04FM1061LBLB

NDC 0116-1061-18

DYNA-HEX 4®

Chlorhexidine Gluconate 4% Solution

Antiseptic

Contains:

4% Chlorhexidine Gluconate

Distributed By:

Xttrium Laboratories, Inc.

Mount Prospect, IL 60056

FOR EXTERNAL USE ONLY

Net Contents: 18 fl oz (532mL)

4DY18FM1061LBLB